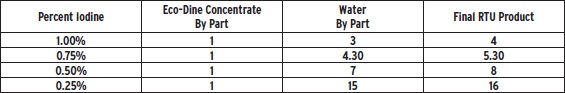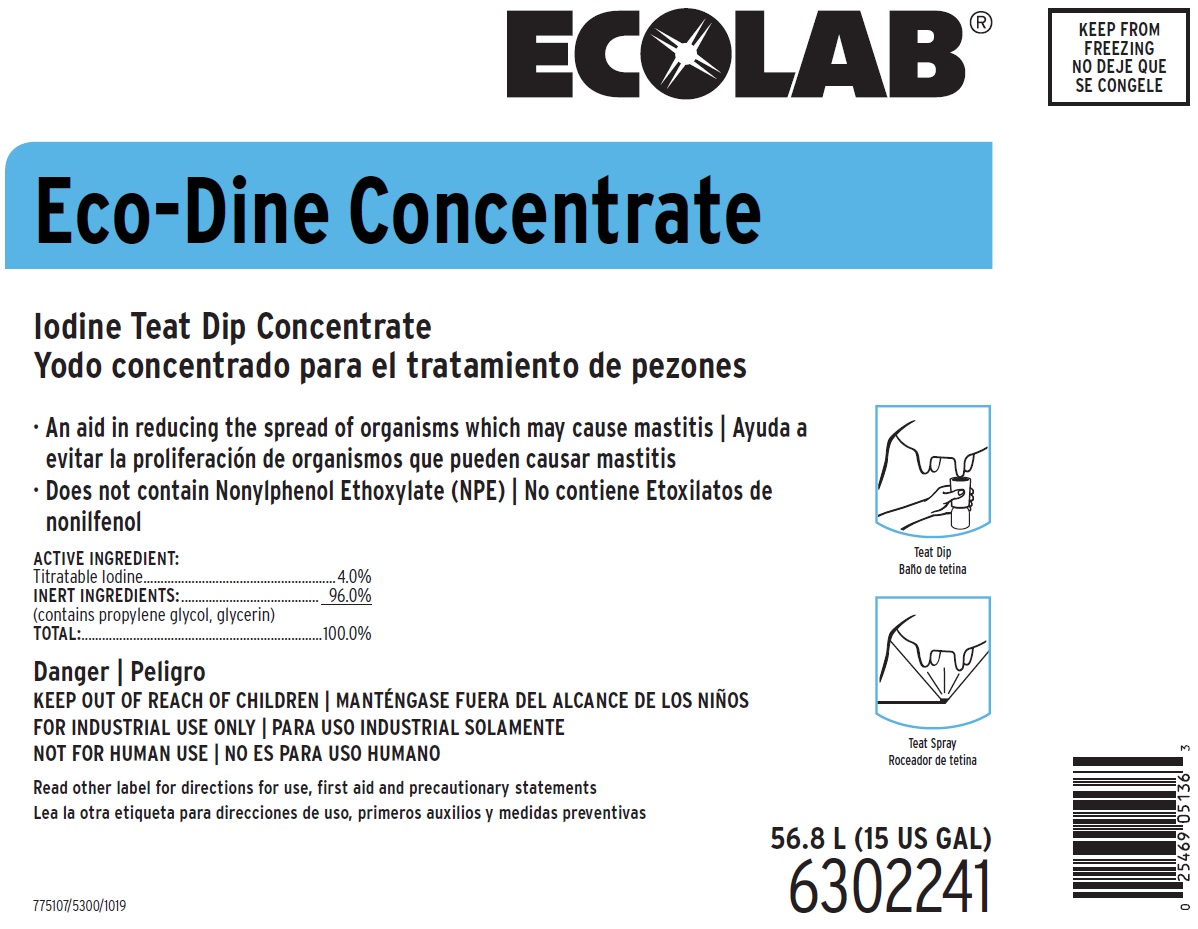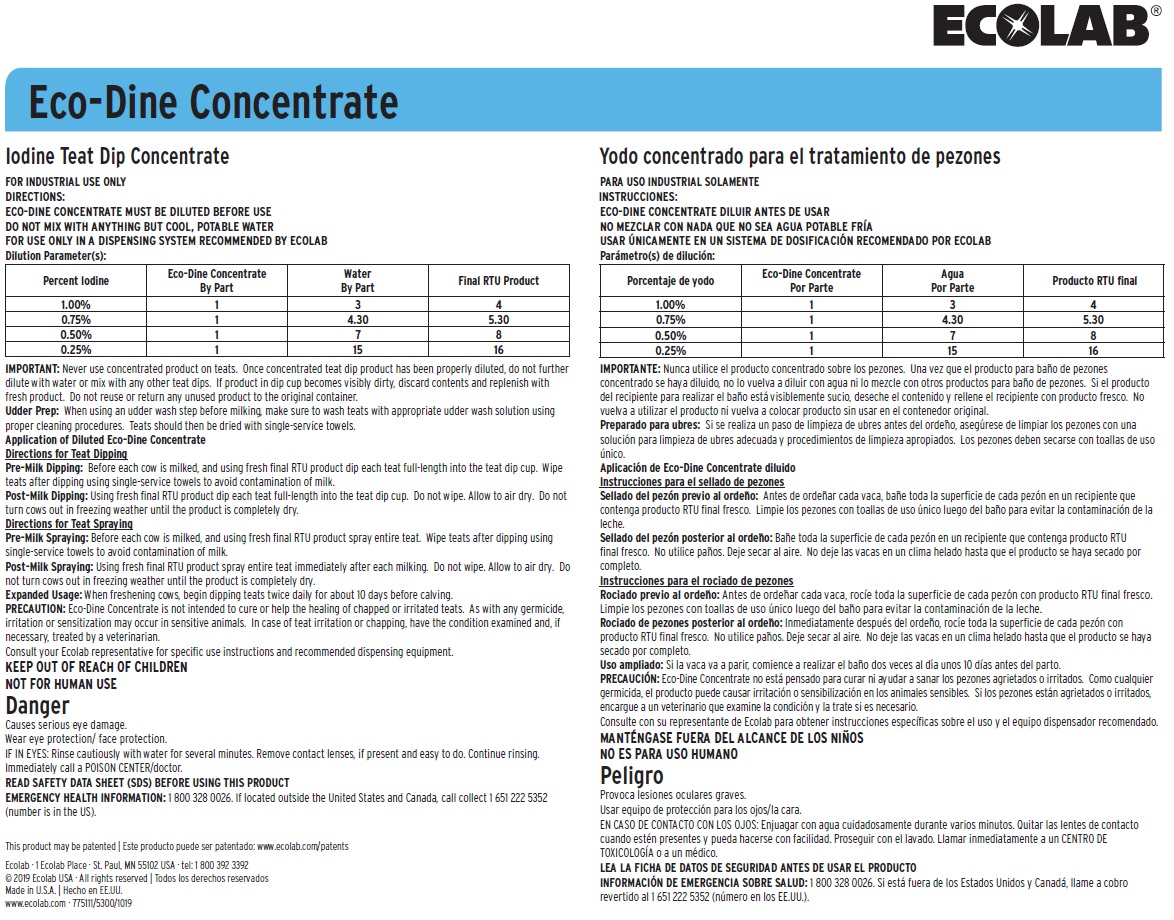 DRUG LABEL: Eco-Dine Concentrate
NDC: 47593-616 | Form: SOLUTION, CONCENTRATE
Manufacturer: Ecolab Inc.
Category: animal | Type: OTC ANIMAL DRUG LABEL
Date: 20210928

ACTIVE INGREDIENTS: IODINE 40 mg/1 mL

KEEP OUT OF REACH OF CHILDREN

NOT FOR HUMAN USE

Danger

Causes serious eye damage.

Wear eye protection/ face protection.

IF IN EYES: Rinse cautiously with water for several minutes. Remove contact lenses, if present and easy to do. Continue rinsing. Immediately call a POISON CENTER/doctor.

DIRECTIONS:

ECO-DINE CONCENTRATE MUST BE DILUTED BEFORE USE

DO NOT MIX WITH ANYTHING BUT COOL, POTABLE WATER

FOR USE ONLY IN A DISPENSING SYSTEM RECOMMENDED BY ECOLAB Dilution Parameter(s):

IMPORTANT: Never use concentrated product on teats. Once concentrated teat dip product has been properly diluted, do not further dilute with water or mix with any other teat dips. If product in dip cup becomes visibly dirty, discard contents and replenish with fresh product. Do not reuse or return any unused product to the original container.

Udder Prep: When using an udder wash step before milking, make sure to wash teats with appropriate udder wash solution using proper cleaning procedures. Teats should then be dried with single-service towels.

Application of Diluted Eco-Dine Concentrate

Directions for Teat Dipping

Pre-Milk Dipping: Before each cow is milked, and using fresh final RTU product dip each teat full-length into the teat dip cup. Wipe teats after dipping using single-service towels to avoid contamination of milk.

Post-Milk Dipping: Using fresh final RTU product dip each teat full-length into the teat dip cup. Do not wipe. Allow to air dry. Do not turn cows out in freezing weather until the product is completely dry.

Directions for Teat Spraying

Pre-Milk Spraying: Before each cow is milked, and using fresh final RTU product spray entire teat. Wipe teats after dipping using single-service towels to avoid contamination of milk.

Post-Milk Spraying: Using fresh final RTU product spray entire teat immediately after each milking. Do not wipe. Allow to air dry. Do not turn cows out in freezing weather until the product is completely dry.

Expanded Usage: When freshening cows, begin dipping teats twice daily for about 10 days before calving.

PRECAUTION: Eco-Dine Concentrate is not intended to cure or help the healing of chapped or irritated teats. As with any germicide, irritation or sensitization may occur in sensitive animals. In case of teat irritation or chapping, have the condition examined and, if necessary, treated by a veterinarian.

Consult your Ecolab representative for specific use instructions and recommended dispensing equipment.

OTHER SAFETY INFORMATION

READ SAFETY DATA SHEET (SDS) BEFORE USING THIS PRODUCT

EMERGENCY HEALTH INFORMATION: 1 800 328 0026. If located outside the United States and Canada, call collect 1 651 222 5352

(number is in the US).

Principal display panel and representative label

ECOLAB

Eco-Dine Concentrate

Iodine Teat Dip Concentrate

An aid in reducing the spread of organisms which may cause mastitis | Ayuda a evitar la proliferación de organismos que pueden causar mastitis

Does not contain Nonylphenol Ethoxylate (NPE) | No contiene Etoxilatos de nonilfenol

ACTIVE INGREDIENT:

Titratable Iodine.........................................................4.0%

INERT INGREDIENTS:......................................... 96.0%

(contains propylene glycol, glycerin)

TOTAL:......................................................................100.0%

56.8 L (15 US GAL)

6302241

775107/5300/1019

This product may be patented | www.ecolab.com/patents

Ecolab · 1 Ecolab Place · St. Paul, MN 55102 USA · tel: 1 800 392 3392

© 2019 Ecolab USA · All rights reserved

Made in U.S.A.

www.ecolab.com · 775111/5300/1019